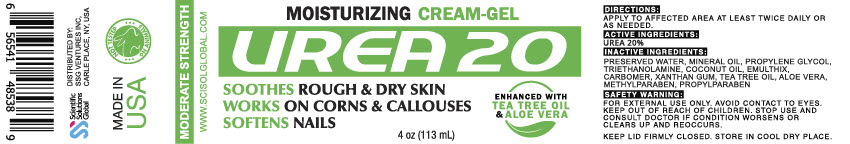 DRUG LABEL: Urea 20
NDC: 81376-210 | Form: GEL
Manufacturer: SSG Ventures Inc
Category: otc | Type: HUMAN OTC DRUG LABEL
Date: 20210407

ACTIVE INGREDIENTS: UREA 20 g/100 mL
INACTIVE INGREDIENTS: TROLAMINE; ALOE VERA LEAF; CARBOMER HOMOPOLYMER, UNSPECIFIED TYPE; XANTHAN GUM; MINERAL OIL; COCONUT OIL; WATER; TEA TREE OIL; PROPYLENE GLYCOL; PROPYLPARABEN; METHYLPARABEN

Urea 20

PACKAGE LABEL

Inactive Ingredients

PRESERVED WATER, MINERAL OIL, PROPYLENE GLYCOL, TRIETHANOLAMINE, COCONUT OIL, EMULTHIX, CARBOMER, XANTHAN GUM, TEA TREE OIL, ALOE VERA, METHYLPARABEN, PROPYLPARABEN

Inactive Ingredients

CARBOMER, XANTHAN GUM, MINERAL OIL, PROPYLENE
GLYCOL, EMULSIFIERS, TRIETHANOLOAMINE

Directions

APPLY TO AFFECTED AREA AT LEAST TWICE DAILY OR
AS NEEDED. USE CONTINUOUSLY FOR 2-3 WEEKS FOR
OPTIMAL RESULTS.

Active Ingredients

UREA 20%

DIRECTIONS:

APPLY TO AFFECTED AREA AT LEAST TWICE DAILY OR AS NEEDED.USE CONTINUOUSLY FOR 2-3 WEEKS FOR OPTIMAL RESULTS.

Indications:

SOOTHES ROUGH & DRY SKINSOFTEN NAILSMOISTURIZING GEL

KEEP OUT OF REACH OF CHILDREN.

ACTIVE INGREDIENT

UREA

PURPOSE

REDUCES CORNS & CALLUSES

SAFETY WARNING :

FOR EXTERNAL USE ONLY. AVOID CONTACT TO EYES.STOP USE AND CONSULT DOCTOR IF CONDITION WORSENS OR CLEARS UP AND REOCCURS.